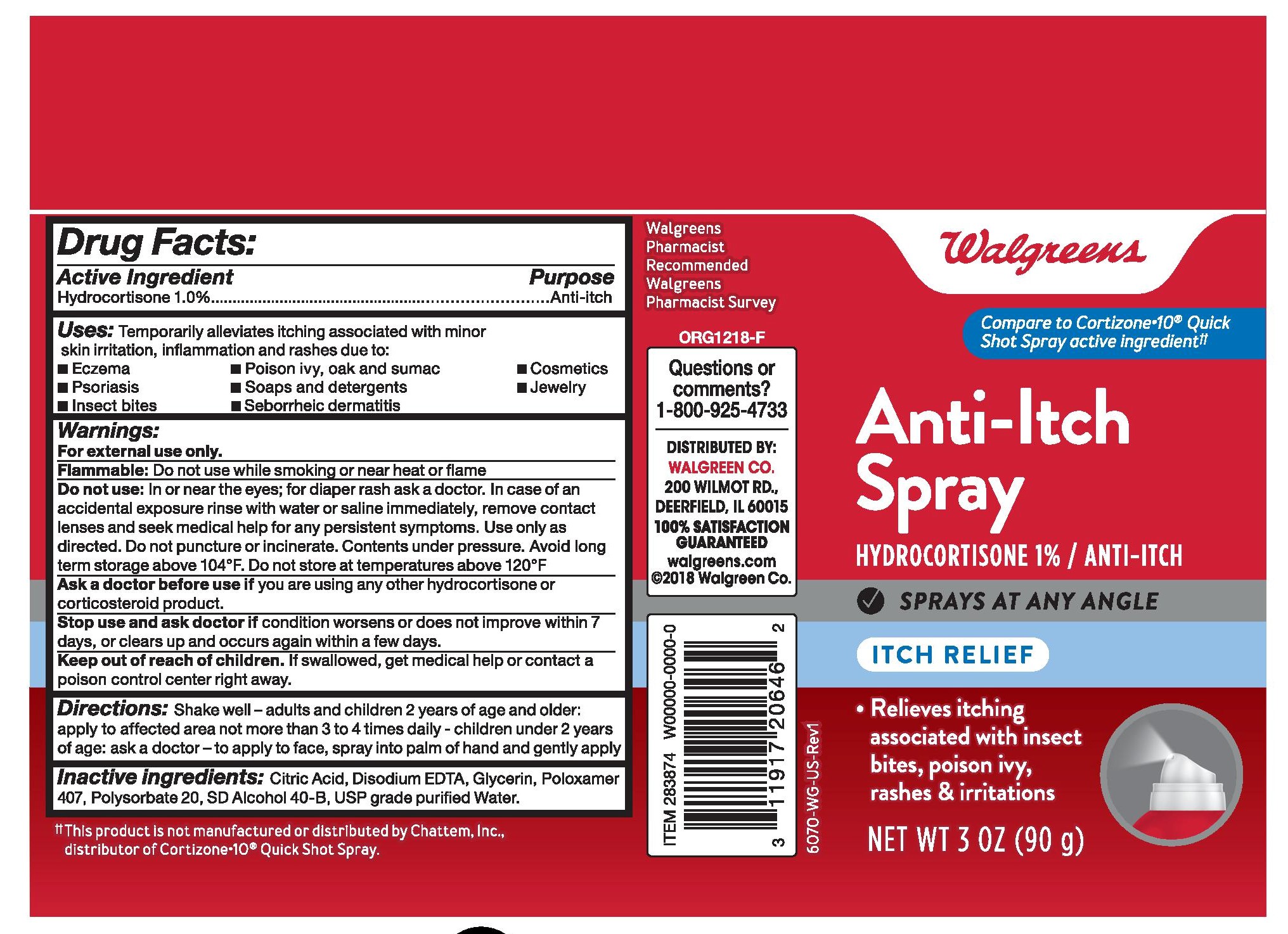 DRUG LABEL: Cooling Itch Relief
NDC: 13709-310 | Form: SPRAY
Manufacturer: NeilMed Pharmaceuticals, Inc
Category: otc | Type: HUMAN OTC DRUG LABEL
Date: 20240111

ACTIVE INGREDIENTS: HYDROCORTISONE 1 g/100 g
INACTIVE INGREDIENTS: GLYCERIN 1 g/100 g

Cooling Itch Relief Spray

OTC Active Ingredient Section

Hydrocortisone 1% Anti itch

Principal Display Panel Anti Itch Spray.jpg

USES

Temporarily relieves itching associated with minorskin irritation and rashes due to:• eczema • poison ivy, oak and sumac • cosmetics• psoriasis • soaps and detergents • jewelry• insect bites • seborrheic dermatitis

WARNINGS

For external use only

DO NOT USE

• in or near the eyes • for external genital • vaginal or anal itching • for diaper rash: ask a doctor

WHEN USING THIS PRODUCT

• Keep out of eyes. Rinse with water to remove • Use only as directed. • Do not puncture or incinerate. Contents under pressure• Do not store at temperature above 120F

STOP USE AND ASK A DOCTOR IF

• condition worsens or does not improve withing 7 days• symptomspersist more than 7 days or clear up and occur again within a few days

KEEP OUT OF REACH OF THE CHILDREN

If swallowed, get medical help or contact a Poison Control Center right away

INACTIVE INGREDIENT

Citric Acid, Disodium EDTA, Glycerin, Poloxamer 407, Polysorbate 20, SD Alcohol 40-B, Water

Dosage and Administration

See Attached Image File Principal Display Panel Anti Itch Spray

Indication & Usage

For the temporary relief of itching associated with minor
skin irritation and rashes due to: • eczema • poison ivy, oak and
sumac • cosmetics • jewelry • soaps and detergents • insect
bites. Other uses of this product should be only under the advice
and supervision of a doctor.

Warnings
For external use only.
Flammable: Keep away from fire or flame
Avoid contact with the eyes. If condition worsens, or if symptoms
persist for more than 7 days or clear up and occur again within a
few days, stop use of this product and do not begin use of any
other hydrocortisone product unless you have consulted a doctor.
Do not use for the treatment of diaper rash. Consult a doctor.
Do not puncture or incinerate. Contents under pressure. Do not
store at temperatures above 120˚F

OTC - Keep Out of Reach of Children

Keep out of reach of the children

If swallowed, get medical help or contact a Poison Control Center right away